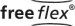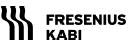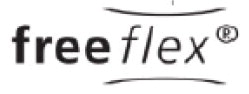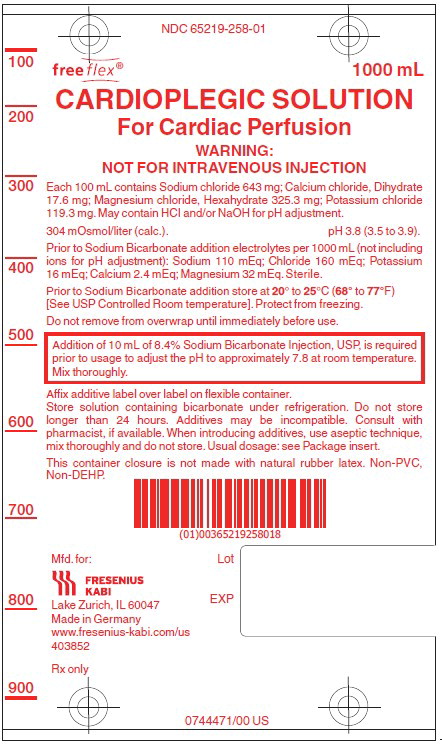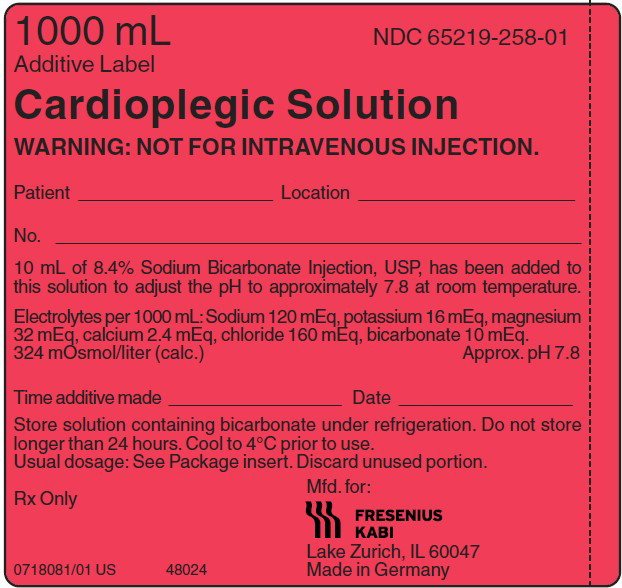 DRUG LABEL: Cardioplegic Solution
NDC: 65219-258 | Form: INJECTION, SOLUTION
Manufacturer: Fresenius Kabi, USA, LLC
Category: prescription | Type: HUMAN PRESCRIPTION DRUG LABEL
Date: 20220527

ACTIVE INGREDIENTS: POTASSIUM CHLORIDE 119.3 mg/100 mL; SODIUM CHLORIDE 643 mg/100 mL; CALCIUM CHLORIDE 17.6 mg/100 mL; MAGNESIUM CHLORIDE 325.3 mg/100 mL
INACTIVE INGREDIENTS: HYDROCHLORIC ACID; SODIUM HYDROXIDE; WATER

CARDIOPLEGIC SOLUTION FOR CARDIAC PERFUSION
NOT FOR INTRAVENOUS INJECTION
Flexible Plastic Container

Rx Only

DESCRIPTION

Cardioplegic Solution is a sterile, nonpyrogenic, essentially isotonic, formulation of electrolytes in water for injection. It is a "core solution" intended for use only after addition of sodium bicarbonate to adjust pH prior to administration. After buffering with sodium bicarbonate it is suitable for cardiac instillation (usually with hypothermia) to induce arrest during open heart surgery. Other agents may be added to the solution prior to instillation (See INSTRUCTIONS FOR USE).

Each 100 mL of solution contains calcium chloride, dihydrate 17.6 mg, magnesium chloride, hexahydrate 325.3 mg, potassium chloride 119.3 mg and sodium chloride 643 mg in water for injection. May contain HCl or NaOH for pH adjustment. Electrolyte content per liter (not including ions for pH adjustment): Calcium (Ca^++) 2.4 mEq; magnesium (Mg^++) 32 mEq; potassium (K^+) 16 mEq; sodium (Na^+) 110 mEq; chloride (Cl‾) 160 mEq. Osmolar concentration, 304 mOsmol/liter (calc.); pH 3.8 (3.5 to 3.9) prior to sodium bicarbonate addition.

It is required that 10 mL (840 mg) of 8.4% Sodium Bicarbonate Injection, USP (10 mEq each of sodium and bicarbonate) be added aseptically and thoroughly mixed with each 1000 mL of cardioplegic solution to adjust pH. Use 10 mL of 8.4% Sodium Bicarbonate Injection, USP, to achieve the approximate pH of 7.8 when measured at room temperature. Use of any other Sodium Bicarbonate Injection may not achieve this pH due to the varying pH's of Sodium Bicarbonate Injections. Due to its inherent instability with other components, sodium bicarbonate must be added just prior to administration. After this addition, the solution must be stored under refrigeration and be used within 24 hours.

The buffered admixture contains the following electrolytes (per liter): Ca^++ 2.4 mEq, Mg^++ 32 mEq, K^+ 16 mEq, Na^+ 120 mEq, Cl‾ 160 mEq and bicarbonate (HCO3‾) 10 mEq; osmolar concentration, 324 mOsmol/liter (calc.); pH 7.8 (approx.). If other agents are added, these values may be altered.

The solution contains no bacteriostat, or antimicrobial agent and is intended only for use (after adjusting pH with sodium bicarbonate) in a single operative procedure. When smaller amounts are required, the unused portion should be discarded.

Cardioplegic Solution with added sodium bicarbonate used as a coronary artery infusate induces cardiac arrest, combats ischemic ionic disturbances, buffers ischemic acidosis and protects energy sources for functional recovery after ischemia.

Calcium Chloride, USP is chemically designated calcium chloride, dihydrate (CaCl2 • 2 H2O), white fragments or granules freely soluble in water.

Magnesium Chloride, USP is chemically designated magnesium chloride, hexahydrate (MgCl2 • 6 H2O), deliquescent flakes or crystals very soluble in water.

Potassium Chloride, USP is chemically designated KCl, a white granular powder freely soluble in water.

Sodium Chloride, USP is chemically designated NaCl, a white crystalline powder freely soluble in water.

Water for Injection, USP is chemically designated H2O.

The flexible plastic container is fabricated from a specially formulated non-plasticized, film containing polypropylene and thermoplastic elastomers (freeflex® bag). Water can permeate from inside the container into the overwrap but not in amounts sufficient to affect the solution significantly. Solutions in contact with the plastic container may leach out certain chemical components from the plastic in very small amounts; however, biological testing was supportive of the safety of the plastic container materials. Exposure to temperatures above 25°C/77°F during transport and storage will lead to minor losses in moisture content. Higher temperatures lead to greater losses. It is unlikely that these minor losses will lead to clinically significant changes within the expiration period.

CLINICAL PHARMACOLOGY

Cardioplegic Solution with added sodium bicarbonate when cooled and instilled into the coronary artery vasculature, causes prompt arrest of cardiac electromechanical activity, combats intracellular ion losses and buffers ischemic acidosis. When used with hypothermia and ischemia, the action may be characterized as cold ischemic potassium-induced cardioplegia. This is conducive to providing the surgeon with a quiet, relaxed heart and bloodless field of operation.

Calcium (Ca^++) ion in low concentration is included in the solution to maintain integrity of cell membrane to ensure that there is no likelihood of calcium paradox during reperfusion.

Magnesium (Mg^++) ion may help stabilize the myocardial membrane by inhibiting a myosin phosphorylase, which protects adenosine triphosphate (ATP) reserves for postischemic activity. The protective effects of magnesium and potassium have been shown to be additive.

Potassium (K^+) ion concentration is responsible for prompt cessation of mechanical myocardial contractile activity. The immediacy of the arrest thus preserves energy supplies for postischemic contractile activity in diastole.

The chloride (Cl‾) and sodium (Na^+) ions have no specific role in the production of cardiac arrest. Sodium is essential to maintain ionic integrity of myocardial tissue. The chloride ions are present to maintain the electroneutrality of the solution.

Added bicarbonate (HCO3‾) anion is included as a buffer to render the solution slightly alkaline and compensate for the metabolic acidosis that accompanies ischemia.

Extemporaneous alternative buffering to the described formulation of this solution is not recommended.

INDICATIONS AND USAGE

Cardioplegic Solution when suitably buffered in combination with ischemia and hypothermia is used to induce cardiac arrest during open heart surgery.

CONTRAINDICATIONS

Cardioplegic Solution must not be administered without the addition of 8.4% Sodium Bicarbonate Injection, USP.

NOT FOR INTRAVENOUS INJECTION.

This solution is only for instillation into cardiac vasculature after buffering with sodium bicarbonate.

WARNINGS

This solution should be used only by those trained to perform open heart surgery. This solution is intended only for use during cardiopulmonary bypass when the coronary circulation is isolated from the systemic circulation (See INDICATIONS AND USAGE).

Do not instill the solution into the coronary vasculature unless sodium bicarbonate has been added. If large volumes of cardioplegic solution are infused and allowed to return to the heart lung machine without any venting from the right heart, then plasma magnesium and potassium levels may rise. Development of severe hypotension and metabolic acidosis while on bypass has been reported when large volumes (8 to 10 liters) of solution are instilled and allowed to enter the pump and then the systemic circulation. Right heart venting is therefore recommended. The buffered solution with added sodium bicarbonate should be cooled to 4°C prior to administration and used within 24 hours of mixing.

PRECAUTIONS

Myocardial temperature should be monitored during surgery to maintain hypothermia.

Continuous electrocardiogram monitoring is essential to detect changes in myocardial activity during the procedure. Appropriate equipment to defibrillate the heart following cardioplegia should be readily available.

Inotropic support drugs should be available during postoperative recovery.

Do not administer unless solution is clear and container is undamaged. Discard unused portion.

Drug Interactions

Additives may be incompatible. Consult with pharmacist, if available. When introducing additives, use aseptic technique, mix thoroughly and do not store (See INSTRUCTIONS FOR USE).

PREGNANCY

Pregnancy: Animal reproduction studies have not been conducted with Cardioplegic Solution. It is also not known whether this solution can cause fetal harm when administered to a pregnant woman or can affect reproduction capacity. Cardioplegic Solution should be given to a pregnant woman only if clearly needed.

Pediatric Use

Safety and effectiveness in pediatric patients have not been established. Because of differences in structure, function, and metabolism, clinical myocardial protection strategies and Cardioplegia solutions that are effective in adult hearts may be less effective in the immature heart.

Geriatric Use

Clinical studies of Cardioplegic Solution did not include sufficient numbers of subjects aged 65 and over to determine whether they responded differently from younger subjects. Other reported clinical experience has not identified differences in responses between older and younger patients.

In general, dose selection for an elderly patient should be cautious, usually starting at the low end of the dosage range reflecting the greater frequency of decreased hepatic, renal, or cardiac function, and of concomitant disease.

This product is unique in that there is no hepatic or renal excretion and specific adjustments for dosing in the elderly are not known.

ADVERSE REACTIONS

Intraoperative and perioperative potential hazards of open heart surgery include myocardial infarction, electrocardiographic abnormalities, and arrhythmias, including ventricular fibrillation. Spontaneous recovery after cardioplegic cardiac arrest may be delayed or absent when circulation is restored. Defibrillation by electric shock may be required to restore normal cardiac function.

To report SUSPECTED ADVERSE REACTIONS, contact Fresenius Kabi USA, LLC at 1-800-551-7176 or FDA at 1-800-FDA-1088 or www.fda.gov/medwatch.

OVERDOSAGE

Overzealous instillation of the solution may result in unnecessary dilatation of the myocardial vasculature and leakage into the perivascular myocardium, possibly causing tissue edema (See WARNINGS, PRECAUTIONS, and ADVERSE REACTIONS).

DOSAGE AND ADMINISTRATION

The following information is suggested as a guide and is subject to variation according to the preference and experience of the surgeon.

It is required that 10 mL (840 mg) of 8.4% Sodium Bicarbonate Injection, USP (10 mEq each of sodium and bicarbonate) be added aseptically and thoroughly mixed with each 1000 mL of cardioplegic solution to adjust pH. Use 10 mL of 8.4% Sodium Bicarbonate Injection, USP, to achieve the approximate pH of 7.8 when measured at room temperature. Use of any other Sodium Bicarbonate Injection may not achieve this pH due to the varying pH's of Sodium Bicarbonate Injections. Due to its inherent instability with other components, sodium bicarbonate must be added just prior to administration. After this addition, the solution must be used within 24 hours. The solution should be cooled to 4°C prior to use.

Following institution of cardiopulmonary bypass at perfusate temperatures of 28° to 30°C, and after cross-clamping of the ascending aorta, the buffered solution is administered by rapid infusion into the aortic root. The initial rate of infusion may be 300 mL/m^2/minute (about 540 mL/min in a 5'8", 70 kg adult with 1.8 square meters of surface area) given for a period of two to four minutes. Concurrent external cooling (regional hypothermia of the pericardium) may be accomplished by instilling a refrigerated (4°C) physiologic solution such as Normosol®-R (balanced electrolyte replacement solution) or Ringer's Injection, USP into the chest cavity.

Should myocardial electromechanical activity persist or recur, the solution may be reinfused at a rate of 300 mL/m^2/min for a period of two minutes. Reinfusion of the solution may be repeated every 20 to 30 minutes or sooner if myocardial temperature rises above 15° to 20°C or returning cardiac activity is observed. The regional hypothermia solution around the heart also may be replenished continuously or periodically in order to maintain adequate hypothermia. Suction may be used to remove warmed infusates. An implanted thermistor probe may be used to monitor myocardial temperature.

The volumes of solution instilled into the aortic root may vary depending on the duration or type of open heart surgical procedure.

Parenteral drug products should be inspected visually for particulate matter and discoloration prior to administration, whenever solution and container permit (See PRECAUTIONS).

INSTRUCTIONS FOR USE

Flexible Plastic Container (freeflex® bag)

Do not remove solution container from its overwrap until immediately before use.

The intact port cap provides visual tamper evidence. Do not use if port cap is prematurely removed. Maintain strict aseptic technique during handling.

To Open

1. Always inspect the solution container before and after removal from the overwrap.
2. Place the solution container on a clean, flat surface. Remove the solution container from the overwrap.
3. Check the solution container for leaks by squeezing firmly. If leaks are found, discard.

To add 10 mL of 8.4% Sodium Bicarbonate Injection, USP, and if other supplemental medication is desired, follow directions below before preparing for administration.

To Add Medication

1. Identify WHITE Additive Port with arrow pointing toward solution container.
2. Immediately before injecting additives, break off WHITE Additive Port Cap with the arrow pointing toward solution container.
3. Hold base of WHITE Additive Port.
4. Using aseptic technique, insert needle (18 to 23 gauge) through the center of WHITE Additive Port's septum and inject additives.
5. Mix solution container contents thoroughly.

Preparation for Administration

(Use aseptic technique)

1. Close the flow control clamp of the administration set.
2. Immediately before inserting the administration set, break off BLUE Infusion Port Cap with the arrow pointing away from solution container.
3. Hold the base of BLUE Infusion Port, twist and push the spike until the spike is fully inserted. NOTE: See full directions accompanying administration set.
4. The BLUE infusion port contains a self‐sealing septum that helps prevent leakage after removing the spike. The infusion port is not intended to be spiked more than once.
5. Suspend solution container from hanger hole.
6. Squeeze and release drip chamber to establish proper fluid level in chamber.
7. Attach aortic infusion device to set.
8. Open flow control clamp to expel air from set and aortic infusion device. Close clamp.
9. Position aortic infusion device to introduce solution into aortic root.
10. Regulate rate of administration with flow control clamp.
11. For Single use Only. Discard unused portion.

HOW SUPPLIED

Cardioplegic Solution is supplied (without sodium bicarbonate) in a single-dose 1000 mL freeflex® plastic container as follows:

Product Code | Unit of Use | Unit of Sale
258810 | NDC 65219-258-01 One 1000 mL freeflex® bag | NDC 65219-258-10 Package of 10 freeflex® bags

WARNING: Do not use flexible container in series connections.

Store at 20° to 25°C (68° to 77°F). [See USP Controlled Room Temperature.] Protect from freezing.

The container closure is not made with natural rubber latex. Non-PVC, Non-DEHP, Sterile.

Manufactured for:

Lake Zurich, Illinois 60047

Made in Germany

451744
www.fresenius-kabi.com/us

Issued: April 2022

PACKAGE LABEL

PACKAGE LABEL - PRINCIPAL DISPLAY – Cardioplegic Solution for Cardiac Perfusion 1000 mL Bag Label

NDC 65219-258-01

1000 mL

CARDIOPLEGIC SOLUTION

For Cardiac Perfusion

WARNING:

NOT FOR INTRAVENOUS INJECTION

PACKAGE LABEL - PRINCIPAL DISPLAY – Cardioplegic Solution Additive Label

1000 mL NDC 65219-258-01

Additive Label

Cardioplegic Solution

WARNING: NOT FOR INTRAVENOUS INJECTION.